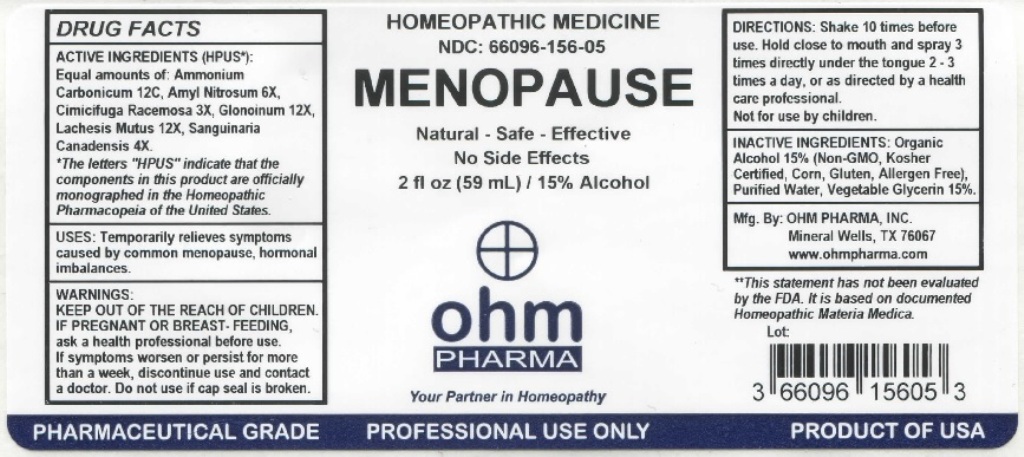 DRUG LABEL: OHM Menopause
NDC: 66096-156 | Form: LIQUID
Manufacturer: OHM PHARMA INC.
Category: homeopathic | Type: HUMAN OTC DRUG LABEL
Date: 20211229

ACTIVE INGREDIENTS: AMMONIUM CARBONATE 12 [hp_C]/59 mL; AMYL NITRITE 6 [hp_X]/59 mL; BLACK COHOSH 3 [hp_X]/59 mL; NITROGLYCERIN 12 [hp_X]/59 mL; LACHESIS MUTA VENOM 12 [hp_X]/59 mL; SANGUINARIA CANADENSIS ROOT 4 [hp_X]/59 mL
INACTIVE INGREDIENTS: ALCOHOL; WATER; GLYCERIN

OHM Menopause

ACTIVE INGREDIENT

ACTIVE INGREDIENTS (HPUS*): Equal amounts of: Ammonium Carbonicum 12C, Amyl Nitrosum 6X, Cimicifuga Racemosa 3X, Glonoinum 12X, Lachesis Mutus 12X, Sanguinaria Canadensis 4X.

*The letters "HPUS" indicate that the components in this product are officially monographed in the Homeopathic Pharmacopeia of the United States.

INDICATIONS AND USAGE

USES: Temporarily relieves symptoms caused by common menopause, hormonal imbalances.

** This statement has not been evaluated by the FDA. It is based on documented Homeopathic Materia Medica.

WARNINGS

WARNINGS: IF PREGNANT OR BREAST-FEEDING, ask a health professional before use. If symptoms worsen or persist for more than a week, discontinue use and contact a doctor

- KEEP OUT OF REACH OF CHILDREN.

DOSAGE AND ADMINISTRATION

DIRECTIONS: Shake 10 times before use. Hold close to mouth and spray 3 times directly under the tongue 2-3 times a day, or as directed by a health care professional. Not for use by children.

Do not use if cap seal is broken.

INACTIVE INGREDIENT

INACTIVE INGREDIENTS: Organic Alcohol 15% (Non-GMO, Kosher Certified, Corn, Gluten, Allergen Free), Purified Water, Vegetable Glycerin 15%.

QUESTIONS

Mfg. By: OHM PHARMA, INC. Mineral Wells, TX 76067

www.ohmpharma.com

PACKAGE LABEL

HOMEOPATHIC MEDICINE

NDC:66096-156-05

MENOPAUSE

Natural - Safe - Effective

No Side Effects

2 fl oz (59mL) / 15% Alcohol

PRODUCT OF USA

PURPOSE

Temporarily relieves symptoms caused by common menopause.